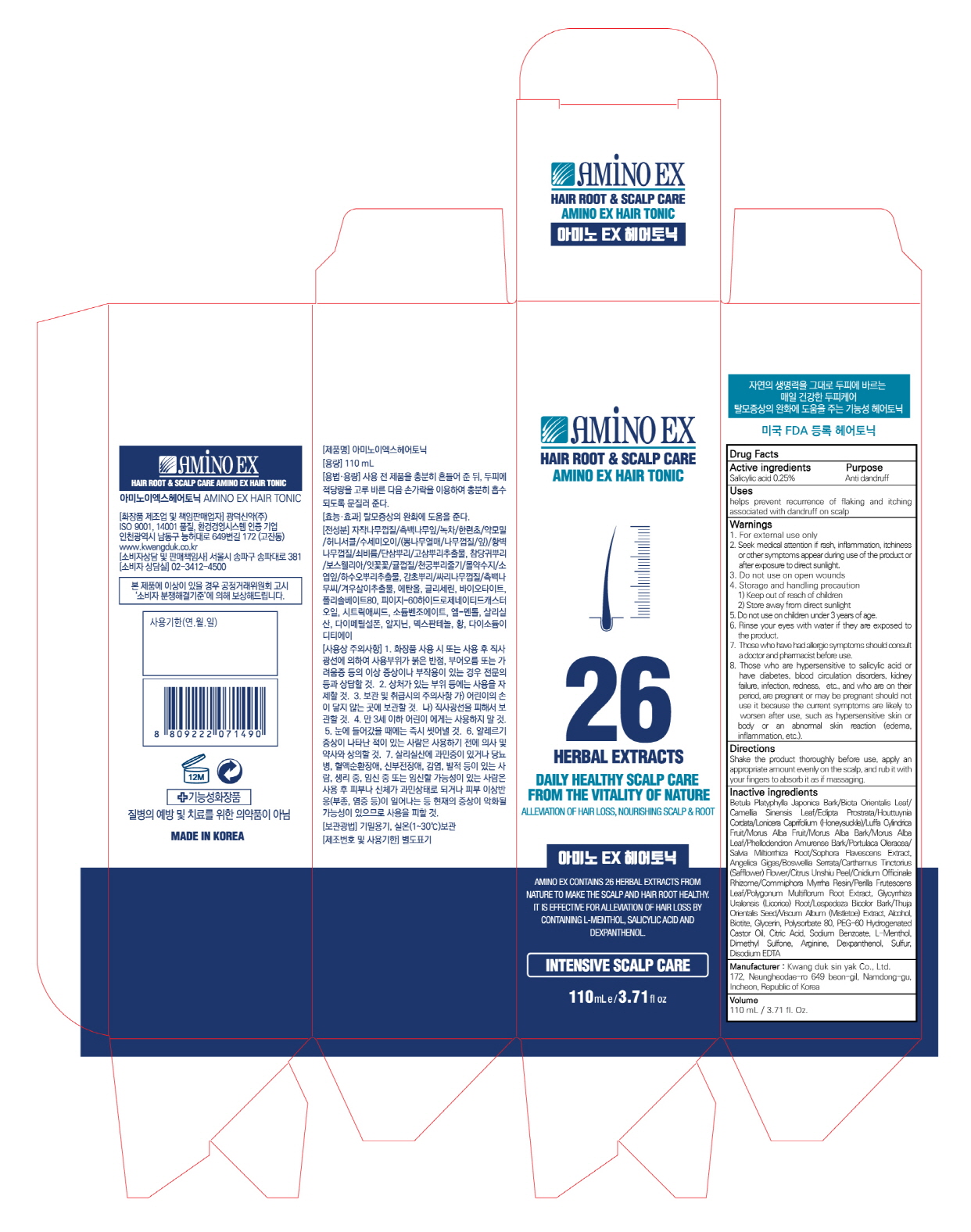 DRUG LABEL: AMINO EX HAIR TONIC
NDC: 71838-0011 | Form: LIQUID
Manufacturer: Kwang Duk Sin Yak Co., Ltd.
Category: otc | Type: HUMAN OTC DRUG LABEL
Date: 20200609

ACTIVE INGREDIENTS: SALICYLIC ACID 0.25 g/100 mL
INACTIVE INGREDIENTS: WATER; LEVOMENTHOL

ACTIVE INGREDIENT

Salicylic acid 0.25%

INACTIVE INGREDIENT

Betula Platyphylla Japonica Bark/Biota Orientalis Leaf/Camellia Sinensis Leaf/EcliptaProstrata/Houttuynia Cordata/Lonicera Caprifolium (Honeysuckle)/Luffa Cylindrica Fruit/MorusAlba Fruit/Morus Alba Bark/Morus Alba Leaf/Phellodendron Amurense Bark/PortulacaOleracea/Salvia Miltiorrhiza Root/Sophora Flavescens Extract, Angelica Gigas/Boswellia Serrata/Carthamus Tinctorius (Safflower) Flower/Citrus UnshiuPeel/Cnidium Officinale Rhizome/Commiphora Myrrha Resin/Perilla Frutescens Leaf/PolygonumMultiflorum Root Extract, Glycyrrhiza Uralensis (Licorice) Root/Lespedeza Bicolor Bark/Thuja Orientalis Seed/ViscumAlbum (Mistletoe) Extract, Alcohol, Biotite, Glycerin, Polysorbate 80, PEG-60 Hydrogenated Castor Oil, Citric Acid, Sodium Benzoate, L-Menthol, Salicylic Acid, Dimethyl Sulfone, Arginine, Dexpanthenol, Sulfur, Disodium EDTA

PURPOSE

helps prevent recurrence of flaking and itching associated with dandruff on scalp

WARNINGS

- For external use only
- Seek medical attention if rash, inflammation, itchiness or other symptoms appear during use of the product or after exposure to direct sunlight.
- Do not use on open wounds
- Storage and handling precaution

1. Keep out of reach of children
2. Store away from direct sunlight

- Do not use on children under 3 years of age.
- Rinse your eyes with water if they are exposed to the product.
- Those who have had allergic symptoms should consult a doctor and pharmacist before use.
- Those who are hypersensitive to salicylic acid or have diabetes, blood circulation disorders, kidney failure, infection, redness, etc., and who are on their period, are pregnant or may be pregnant should not use it because the current symptoms are likely to worsen after use, such as hypersensitive skin or body or an abnormal skin reaction (edema, inflammation, etc.).

KEEP OUT OF REACH OF CHILDREN

INDICATIONS AND USAGE

For external use only

DOSAGE AND ADMINISTRATION

Shake the product thoroughly before use, apply an appropriate amount evenly on the scalp, and rub it with your fingers to absorb it as if massaging.